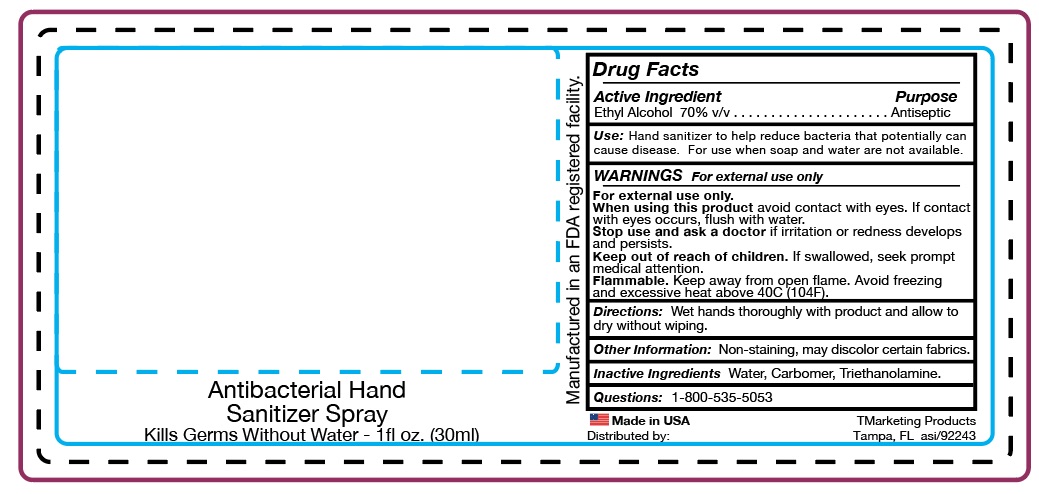 DRUG LABEL: HS
NDC: 58418-156 | Form: SPRAY
Manufacturer: Tropical Enterprises International, Inc.
Category: otc | Type: HUMAN OTC DRUG LABEL
Date: 20200202

ACTIVE INGREDIENTS: ALCOHOL 16.7 g/30 mL
INACTIVE INGREDIENTS: WATER; TRIETHYLAMINE; CARBOMER 940

Formula #LV/64-002 spray_ 70% ethyl alcohol hand sanitizer spray
Iceus formula

ACTIVE INGREDIENT

Ethyl Alcohol 70% v/v

Purpose..... Antiseptic

INDICATIONS AND USAGE

Uses: Hand Sanitizer to reduce bacteria that potentially can cause disease.

For use when soap and water are not available.

updated Use:

Use Hand Sanitizer to help reduce bacteria that potentially can cause disease.

For use when soap and water are not available.

DOSAGE AND ADMINISTRATION

Directions: Wet hands thoroughly with product and allow to dry without wiping.

INACTIVE INGREDIENT

Inactive Ingredients Water, Carbomer, Triethanolamine

WARNING

WARNINGS: For external use only. When using this product avoid contact with eyes. If

contact with eyes occurs, flush with water.

Stop use and ask a doctor if irritation or redness develops and persists.

Keep out of reach of children. If swallowed, seek prompt medical attention.

SAFE HANDLING WARNING

Flammable. Keep away from open flames.

Avoid freezing and excessive heat above 40C (104F)

Questions: 1-800-535-5053

Other Information: Non-staining, may discolor certain fabrics.